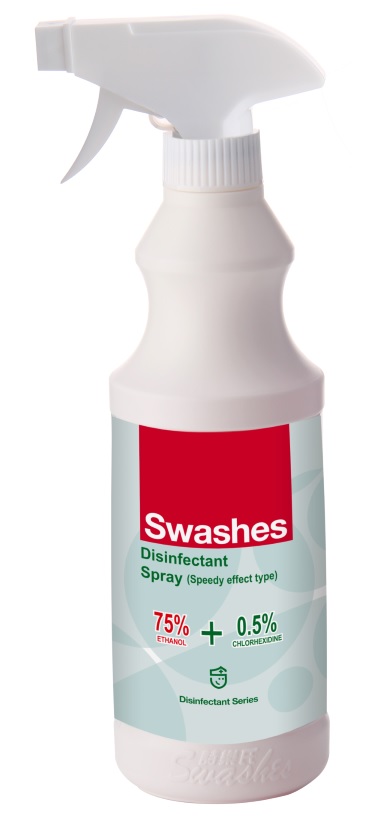 DRUG LABEL: Disinfectant Spray(Speedy effect type)
NDC: 74974-011 | Form: LIQUID
Manufacturer: Swashes (Shenzhen) Co., Ltd.
Category: otc | Type: HUMAN OTC DRUG LABEL
Date: 20200413

ACTIVE INGREDIENTS: CHLORHEXIDINE ACETATE 0.5 g/100 mL; ALCOHOL 63 mL/100 mL
INACTIVE INGREDIENTS: C12-15 PARETH-10; PROPYLENE GLYCOL; GLYCERIN; WATER

Disinfectant Spray(Speedy effect type) 74974-011

Disinfectant Spray(Speedy effect type)

Active Ingredient(s)

Alcohol 63% v/v.

Chlorhexidine acetate 0.5g/100mL

Purpose: Antiseptic

Purpose

Antiseptic, Disinfectant Spray(Speedy effect type)

Use

Disinfect the surface of objects

Warnings

For external use only. Flammable. Keep away from heat or flame

Do not use

- in children less than 2 months of age
- on open skin wounds

When using this product keep out of eyes, ears, and mouth. In case of contact with eyes, rinse eyes thoroughly with water.
Stop use and ask a doctor if irritation or rash occurs. These may be signs of a serious condition.
Keep out of reach of children. If swallowed, get medical help or contact a Poison Control Center right away.

Stop use and ask a doctor if irritation or rash occurs. These may be signs of a serious condition.

Keep out of reach of children. If swallowed, get medical help or contact a Poison Control Center right away.

Directions

- Spray on the surface of the object to disinfect
- Supervise children under 6 years of age when using this product to avoid swallowing.

Other information

- Store between 15-30C (59-86F)
- Avoid freezing and excessive heat above 40C (104F)

Inactive ingredients

1,2-Propanediol
Medicinal Glycerin
Primary Alcobol Ethoxylate
Purity Water

Package Label - Principal Display Panel

500 mL NDC: 74974-011-01